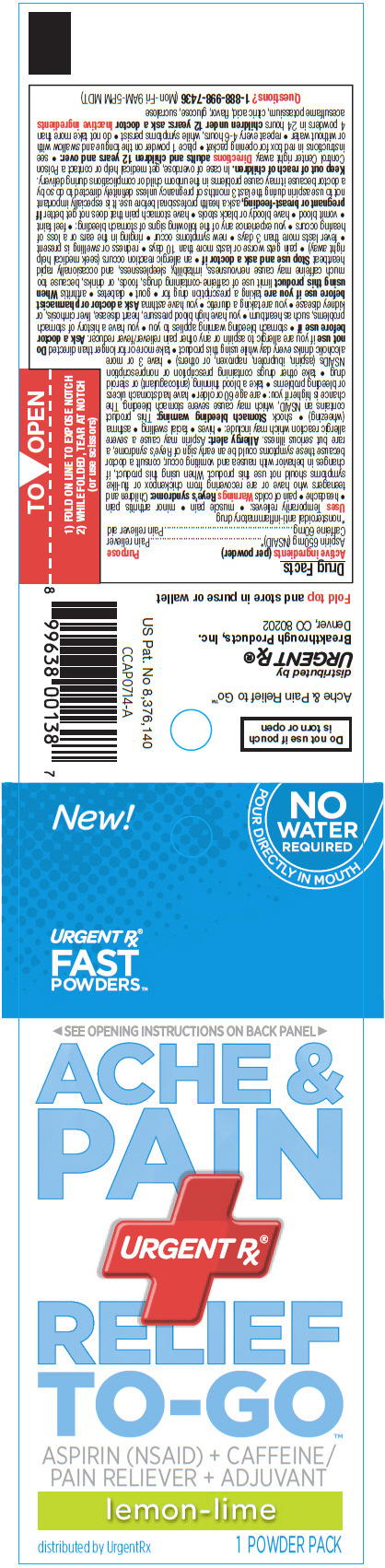 DRUG LABEL: Ache and Pain Relief to Go
NDC: 51596-008 | Form: POWDER
Manufacturer: Breakthrough Products Inc.
Category: otc | Type: HUMAN OTC DRUG LABEL
Date: 20141008

ACTIVE INGREDIENTS: aspirin 650 mg/1 1; caffeine 60 mg/1 1
INACTIVE INGREDIENTS: acesulfame potassium; anhydrous citric acid; dextrose; sucralose

Ache and Pain Relief to Go™

Drug Facts

ACTIVE INGREDIENT

Active ingredients (per powder) | Purpose
Aspirin 650mg (NSAID) [nonsteroidal anti-inflammatory drug] | Pain reliever
Caffeine 60mg | Pain reliever aid

Uses

Temporarily relieves:

- muscle pain
- minor arthritis pain
- headache
- pain of colds

Warnings

Reye's syndrome

Children and teenagers who have or are recovering from chickenpox or flu-like symptoms should not use this product. When using this product, if changes in behavior with nausea and vomiting occur, consult a doctor because these symptoms could be an early sign of Reye's syndrome, a rare but serious illness.

Allergy alert

Aspirin may cause a severe allergic reaction which may include:

- hives
- facial swelling
- asthma (wheezing)
- shock

Stomach bleeding warning

This product contains an NSAID, which may cause severe stomach bleeding. The chance is higher if you:

- are age 60 or older
- have had stomach ulcers or bleeding problems
- take a blood thinning (anticoagulant) or steroid drug
- take other drugs containing prescription or nonprescription NSAIDs (aspirin, ibuprofen, naproxen, or others)
- have 3 or more alcoholic drinks every day while using this product
- take more or for longer than directed

Do not use if you are allergic to aspirin or any other pain reliever/fever reducer.

Ask a doctor before use if

- stomach bleeding warning applies to you
- you have a history of stomach problems, such as heartburn
- you have high blood pressure, heart disease, liver cirrhosis, or kidney disease
- you are taking a diuretic
- you have asthma

Ask a doctor or pharmacist before use if you are taking a prescription drug for

- gout
- diabetes
- arthritis

When using this product limit use of caffeine-containing drugs, foods, or drinks, because too much caffeine may cause nervousness, irritability, sleeplessness, and occasionally rapid heartbeat

Stop use and ask a doctor if

- an allergic reaction occurs (seek medical help right away)
- pain gets worse or lasts more than 10 days
- redness or swelling is present
- fever lasts more than 3 days
- new symptoms occur
- ringing in the ears or a loss of hearing occurs
- you experience any of the following signs of stomach bleeding:
  - feel faint
  - vomit blood
  - have bloody or black stools
  - have stomach pain that does not get better

PREGNANCY OR BREAST FEEDING

If pregnant or breast-feeding, ask a health professional before use. It is especially important not to use aspirin during the last 3 months of pregnancy unless definitely directed to do so by a doctor because it may cause problems in the unborn child or complications during delivery.

Keep out of reach of children. In case of overdose, get medical help or contact a Poison Control Center right away.

Directions

adults and children 12 years and over:

- see instructions in red box for opening packet
- place 1 powder on the tongue and swallow with or without water
- repeat every 4-6 hours, while symptoms persist
- do not take more than 4 powders in 24 hours

children under 12 years: ask a doctor

Inactive ingredients

acesulfame potassium, citric acid, flavor, glucose, sucralose

Questions?

1-888-998-7436 (Mon-Fri 9AM-5PM MDT)

Do not use if pouch
is torn or open

distributed by
URGENT Rx®
Breakthrough Products, Inc.
Denver, CO 80202

PRINCIPAL DISPLAY PANEL - 1 Powder Packet

New!

NO
WATER
REQUIRED
POUR DIRECTLY IN MOUTH

URGENT Rx®
FAST
POWDERS™

◀ SEE OPENING INSTRUCTIONS ON BACK PANEL ▶

ACHE &
PAIN
URGENT Rx®
RELIEF
TO-GO™

ASPIRIN (NSAID) + CAFFEINE /
PAIN RELIEVER + ADJUVANT

lemon-lime

distributed by UrgentRx
1 POWDER PACK